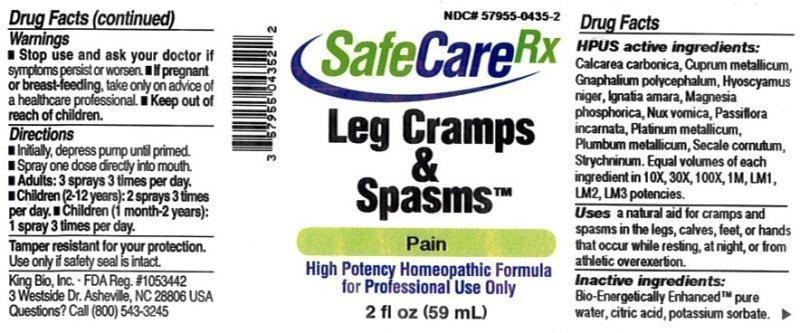 DRUG LABEL: Leg Cramps and Spasms
NDC: 57955-0435 | Form: LIQUID
Manufacturer: King Bio Inc.
Category: homeopathic | Type: HUMAN OTC DRUG LABEL
Date: 20150608

ACTIVE INGREDIENTS: OYSTER SHELL CALCIUM CARBONATE, CRUDE 10 [hp_X]/59 mL; COPPER 10 [hp_X]/59 mL; PSEUDOGNAPHALIUM OBTUSIFOLIUM 10 [hp_X]/59 mL; HYOSCYAMUS NIGER 10 [hp_X]/59 mL; STRYCHNOS IGNATII SEED 10 [hp_X]/59 mL; MAGNESIUM PHOSPHATE, DIBASIC TRIHYDRATE 10 [hp_X]/59 mL; STRYCHNOS NUX-VOMICA SEED 10 [hp_X]/59 mL; PASSIFLORA INCARNATA FLOWERING TOP 10 [hp_X]/59 mL; PLATINUM 10 [hp_X]/59 mL; LEAD 10 [hp_X]/59 mL; CLAVICEPS PURPUREA SCLEROTIUM 10 [hp_X]/59 mL; STRYCHNINE 10 [hp_X]/59 mL
INACTIVE INGREDIENTS: WATER; ANHYDROUS CITRIC ACID; POTASSIUM SORBATE

Leg Cramps and Spasms™

ACTIVE INGREDIENT

Drug Facts__________________________________________________________________________________________________________

HPUS active ingredients: Calcarea carbonica, Cuprum metallicum, Gnaphalium polycephalum, Hyoscyamus niger, Ignatia amara, Magnesia phosphorica, Nux vomica, Passiflora incarnata, Platinum metallicum, Plumbum metallicum, Secale cornutum, Strychninum. Equal volumes of each ingredient in 10X, 30X, 100X, 1M, LM1, LM2, LM3 potencies.

INDICATIONS AND USAGE

Uses a natural aid for cramps and spasms in the legs, calves, feet, or hands that occur while resting, at night, or from athletic overexertion.

Inactive Ingredients:

Bio-Energetically Enhanced™ pure water, citric acid and potassium sorbate.

Warnings

- Stop use and ask your doctor if symptoms persist or worsen.
- If pregnant or breast-feeding, take only on advice of a healthcare professional.

- Keep out of reach of children.

Directions

- Initially, depress pump until primed.
- Spray one dose directly into mouth.
- Adults: 3 sprays 3 times per day.
- Children (2-12 years): 2 sprays 3 times per day.
- Children (1month-2 years): 1 spray 3 times per day.

OTHER SAFETY INFORMATION

Tamper resistant for your protection. Use only if safety seal is intact.

PURPOSE

Uses a natural aid for cramps and spasms in the legs, calves, feet, or hands that occur while resting, at night, or from athletic overexertion.